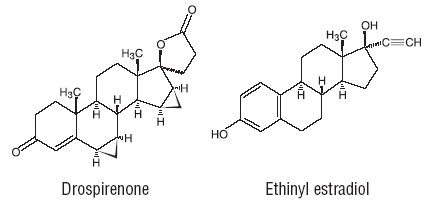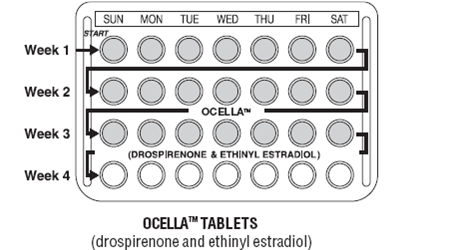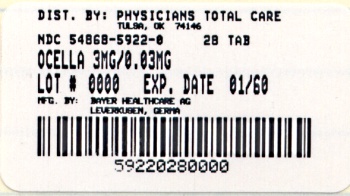 DRUG LABEL: OCELLA
NDC: 54868-5922 | Form: KIT | Route: ORAL
Manufacturer: Physicians Total Care, Inc.
Category: prescription | Type: HUMAN PRESCRIPTION DRUG LABEL
Date: 20110223

ACTIVE INGREDIENTS: DROSPIRENONE 3 mg/1 1; ETHINYL ESTRADIOL 0.03 mg/1 1
INACTIVE INGREDIENTS: STARCH, CORN; FERRIC OXIDE YELLOW; HYPROMELLOSES; LACTOSE MONOHYDRATE; POLYETHYLENE GLYCOL 6000; MAGNESIUM STEARATE; POVIDONE K25; TALC; TITANIUM DIOXIDE; STARCH, CORN; HYPROMELLOSES; LACTOSE MONOHYDRATE; MAGNESIUM STEARATE; POVIDONE K25; TALC; TITANIUM DIOXIDE

OCELLA™ 28 TABLETS
(drospirenone and ethinyl estradiol)

PHYSICIAN LABELING

Rx only

PATIENTS SHOULD BE COUNSELED THAT THIS PRODUCT DOES NOT PROTECT AGAINST HIV INFECTION (AIDS) AND OTHER SEXUALLY TRANSMITTED DISEASES.

Description

OCELLA provides an oral contraceptive regimen consisting of 21 active film coated tablets each containing 3 mg of drospirenone and 0.03 mg of ethinyl estradiol and 7 inert film coated tablets. The inactive ingredients are lactose monohydrate NF, corn starch NF, modified starch NF, povidone 25000 USP, magnesium stearate NF, hydroxylpropylmethyl cellulose USP, macrogol 6000 NF, talc USP, titanium dioxide USP, ferric oxide pigment, yellow NF. The inert film coated tablets contain lactose monohydrate NF, corn starch NF, povidone 25000 USP, magnesium stearate NF, hydroxylpropylmethyl cellulose USP, talc USP, titanium dioxide USP.

Drospirenone (6R,7R,8R,9S,10R,13S,14S,15S,16S,17S)-1,3',4',6,6a,7,8,9,10,11,12,13, 14,15,15a,16-hexadecahydro-10,13-dimethylspiro-[17H-dicyclopropa-6,7:15,16] cyclopenta[ a]phenanthrene-17,2'(5H)-furan]-3,5'(2H)-dione) is a synthetic progestational compound and has a molecular weight of 366.5 and a molecular formula of C24H30O3. Ethinyl estradiol (19-nor-17α-pregna 1,3,5(10)-triene-20-yne-3,17-diol) is a synthetic estrogenic compound and has a molecular weight of 296.4 and a molecular formula of C20H24O2. The structural formulas are as follows:

CLINICAL PHARMACOLOGY

PHARMACODYNAMICS

Combination oral contraceptives (COCs) act by suppression of gonadotropins. Although the primary mechanism of this action is inhibition of ovulation, other alterations include changes in the cervical mucus (which increases the difficulty of sperm entry into the uterus) and the endometrium (which reduces the likelihood of implantation).

Drospirenone is a spironolactone analogue with antimineralocorticoid activity. Preclinical studies in animals and in vitro have shown that drospirenone has no androgenic, estrogenic, glucocorticoid, and antiglucocorticoid activity. Preclinical studies in animals have also shown that drospirenone has antiandrogenic activity.

PHARMACOKINETICS

Absorption

The absolute bioavailability of drospirenone (DRSP) from a single entity tablet is about 76%. The absolute bioavailability of ethinyl estradiol (EE) is approximately 40% as a result of presystemic conjugation and first-pass metabolism. The absolute bioavailability of OCELLA which is a combination tablet of drospirenone and ethinyl estradiol has not been evaluated. Serum concentrations of DRSP and EE reached peak levels within 1–3 hours after administration of OCELLA. After single dose administration of OCELLA, the relative bioavailability, compared to a suspension, was 107% and 117% for DRSP and EE, respectively.

The pharmacokinetics of DRSP are dose proportional following single doses ranging from 1–10 mg. Following daily dosing of OCELLA, steady state DRSP concentrations were observed after 10 days. There was about 2 to 3 fold accumulation in serum Cmax and AUC (0–24h) values of DRSP following multiple dose administration of OCELLA (see TABLE I).

For EE, steady-state conditions are reported during the second half of a treatment cycle. Following daily administration of OCELLA serum Cmax and AUC(0–24h) values of EE accumulate by a factor of about 1.5 to 2.

TABLE I TABLE OF MEAN PHARMACOKINETIC PARAMETERS OF OCELLA (Drospirenone 3 mg and Ethinyl Estradiol 0.03 mg)
Drospirenone
Mean (%CV) Values
Cycle /; Day | No. of; Subjects | Cmax; (ng/mL) | Tmax; (h) | AUC(0–24h); (ng•h/mL) | t1/2; (h)
1/1 | 12 | 36.9 (13) | 1.7 (47) | 288 (25) | NA [NA = Not available]
1/21 | 12 | 87.5 (59) | 1.7 (20) | 827 (23) | 30.9 (44)
6/21 | 12 | 84.2 (19) | 1.8 (19) | 930 (19) | 32.5 (38)
9/21 | 12 | 81.3 (19) | 1.6 (38) | 957 (23) | 31.4 (39)
13/21 | 12 | 78.7 (18) | 1.6 (26) | 968 (24) | 31.1 (36)
Ethinyl Estradiol
Mean (%CV) Values
Cycle /; Day | No. of; Subjects | Cmax; (pg/mL) | Tmax; (h) | AUC(0–24h); (pg•h/mL) | t1/2; (h)
1/1 | 11 | 53.5 (43) | 1.9 (45) | 280.3 (87) | NA
1/21 | 11 | 92.1 (35) | 1.5 (40) | 461.3 (94) | NA
6/21 | 11 | 99.1 (45) | 1.5 (47) | 346.4 (74) | NA
9/21 | 11 | 87 (43) | 1.5 (42) | 485.3 (92) | NA
13/21 | 10 | 90.5 (45) | 1.6 (38) | 469.5 (83) | NA

Effect of Food

The rate of absorption of DRSP and EE following single administration of two OCELLA tablets was slower under fed conditions with the serum Cmax being reduced about 40% for both components. The extent of absorption of DRSP, however, remained unchanged. In contrast the extent of absorption of EE was reduced by about 20% under fed conditions.

Distribution

DRSP and EE serum levels decline in two phases. The apparent volume of distribution of DRSP is approximately 4 L/kg and that of EE is reported to be approximately 4–5 L/kg.

DRSP does not bind to sex hormone binding globulin (SHBG) or corticosteroid binding globulin (CBG) but binds about 97% to other serum proteins. Multiple dosing over 3 cycles resulted in no change in the free fraction (as measured at trough levels). EE is reported to be highly but non-specifically bound to serum albumin (approximately 98.5%) and induces an increase in the serum concentrations of both SHBG and CBG. EE induced effects on SHBG and CBG were not affected by variation of the DRSP dosage in the range of 2 to 3 mg.

Metabolism

The two main metabolites of DRSP found in human plasma were identified to be the acid form of DRSP generated by opening of the lactone ring and the 4,5-dihydrodrospirenone- 3-sulfate. These metabolites were shown not to be pharmacologically active. In in vitro studies with human liver microsomes, DRSP was metabolized only to a minor extent mainly by cytochrome P450 3A4 (CYP3A4).

EE has been reported to be subject to presystemic conjugation in both small bowel mucosa and the liver. Metabolism occurs primarily by aromatic hydroxylation but a wide variety of hydroxylated and methylated metabolites are formed. These are present as free metabolites and as conjugates with glucuronide and sulfate. CYP3A4 in the liver are responsible for the 2-hydroxylation which is the major oxidative reaction. The 2-hydroxy metabolite is further transformed by methylation and glucuronidation prior to urinary and fecal excretion.

Excretion

DRSP serum levels are characterized by a terminal disposition phase half-life of approximately 30 hours after both single and multiple dose regimens. Excretion of DRSP was nearly complete after ten days and amounts excreted were slightly higher in feces compared to urine. DRSP was extensively metabolized and only trace amounts of unchanged DRSP were excreted in urine and feces. At least 20 different metabolites were observed in urine and feces. About 38–47% of the metabolites in urine were glucuronide and sulfate conjugates. In feces, about 17–20% of the metabolites were excreted as glucuronides and sulfates.

For EE the terminal disposition phase half-life has been reported to be approximately 24 hours. EE is not excreted unchanged. EE is excreted in the urine and feces as glucuronide and sulfate conjugates and undergoes enterohepatic circulation.

Special Populations

Race

The effect of race on the disposition of OCELLA has not been evaluated.

Hepatic Dysfunction

OCELLA is contraindicated in patients with hepatic dysfunction (also see BOLDED WARNINGS). The mean exposure to DRSP in women with moderate liver impairment is approximately three times the exposure in women with normal liver function.

Renal Insufficiency

OCELLA is contraindicated in patients with renal insufficiency (also see WARNINGS).

The effect of renal insufficiency on the pharmacokinetics of DRSP (3 mg daily for 14 days) and the effect of DRSP on serum potassium levels were investigated in female subjects (n=28, age 30–65) with normal renal function and mild and moderate renal impairment. All subjects were on a low potassium diet. During the study 7 subjects continued the use of potassium sparing drugs for the treatment of the underlying illness. On the 14th day (steady-state) of DRSP treatment, the serum DRSP levels in the group with mild renal impairment (creatinine clearance CLcr, 50–80 mL/min) were comparable to those in the group with normal renal function (CLcr, >80 mL/min). The serum DRSP levels were on average 37% higher in the group with moderate renal impairment (CLcr, 30–50 mL/min) compared to those in the group with normal renal function. DRSP treatment was well tolerated by all groups. DRSP treatment did not show any clinically significant effect on serum potassium concentration. Although hyperkalemia was not observed in the study, in five of the seven subjects who continued use of potassium sparing drugs during the study, mean serum potassium levels increased by up to 0.33 mEq/L. Therefore, potential exists for hyperkalemia to occur in subjects with renal impairment whose serum potassium is in the upper reference range, and who are concomitantly using potassium sparing drugs.

INDICATIONS AND USAGE

OCELLA is indicated for the prevention of pregnancy in women who elect to use an oral contraceptive.

Oral contraceptives are highly effective. TABLE II lists the typical accidental pregnancy rates for users of combination oral contraceptives and other methods of contraception. The efficacy of these contraceptive methods, except sterilization, depends upon the reliability with which they are used. Correct and consistent use of methods can result in lower failure rates.

TABLE II Percentage of women experiencing an unintended pregnancy during the first year of typical use and first year of perfect use of contraception and the percentage continuing use at the end of the first year: United States.
 | % of Women Experiencing an; Accidental Pregnancy; Within the First Year of Use |  | % of Women; Continuing Use; At One Year
Method; (1) | Typical Use; (2) | Perfect Use; (3) | (4)
Chance | 85 | 85
Spermicides | 26 | 6 | 40
Periodic abstinence | 25 |  | 63
Calendar |  | 9
Ovulation method |  | 3
Sympto-thermal |  | 2
Post-ovulation |  | 1
Withdrawal | 19 | 4
Cap [With spermicidal cream or jelly.]
Parous women | 40 | 26 | 42
Nulliparous women | 20 | 9 | 56
Sponge
Parous women | 40 | 20 | 42
Nulliparous women | 20 | 9 | 56
Diaphragm | 20 | 6 | 56
Condom
Female (Reality) | 21 | 5 | 56
Male | 14 | 3 | 61
Pill | 5 |  | 71
progestin only |  | 0.5
combined |  | 0.1
IUD
Progesterone T: | 2 | 1.5 | 81
Copper T 380A | 0.8 | 0.6 | 78
Lng 20 | 0.1 | 0.1 | 81
Depo Provera | 0.3 | 0.3 | 70
Norplant and Norplant-2 | 0.05 | 0.05 | 88
Female Sterilization | 0.5 | 0.5 | 100
Male Sterilization | 0.15 | 0.1 | 100
Emergency Contraceptive Pills: Treatment initiated within 72 hours after unprotected intercourse reduces the risk of pregnancy by at least 75%
Lactational Amenorrhea Method: LAM is highly effective, temporary method of contraception
Source: Trussell J, Contraceptive efficacy. In Hatcher RA, Trussell J, Stewart F, Cates W, Stewart GK, Kowal D, Guest F, Contraceptive Technology: Seventeenth Revised Edition. New York NY: Irvington Publishers, 1998.

In clinical efficacy studies of OCELLA of up to 2 years duration, 2,629 subjects completed 33,160 cycles of use without any other contraception. The mean age of the subjects was 25.5 ± 4.7 years. The age range was 16 to 37 years. The racial demographic was: 83% Caucasian, 1% Hispanic, 1% Black, <1% Asian, <1% other, <1% missing data, 14% not inquired and <1% unspecified. Pregnancy rates in the clinical trials were less than one per 100 woman-years of use.

CONTRAINDICATIONS

OCELLA should not be used in women who have the following:

- Renal insufficiency
- Hepatic dysfunction
- Adrenal insufficiency
- Thrombophlebitis or thromboembolic disorders
- A past history of deep-vein thrombophlebitis or thromboembolic disorders
- Cerebral-vascular or coronary-artery disease
- Valvular heart disease with thrombogenic complications
- Severe hypertension
- Diabetes with vascular involvement
- Headaches with focal neurological symptoms
- Known or suspected carcinoma of the breast
- Carcinoma of the endometrium or other known or suspected estrogen-dependent neoplasia
- Undiagnosed abnormal genital bleeding
- Cholestatic jaundice of pregnancy or jaundice with prior pill use
- Liver tumor (benign or malignant) or active liver disease
- Known or suspected pregnancy
- Heavy smoking (≥15 cigarettes per day) and over age 35

WARNINGS

BOXED WARNING

Cigarette smoking increases the risk of serious cardiovascular side effects from oral contraceptive use. This risk increases with age and with heavy smoking (15 or more cigarettes per day) and is quite marked in women over 35 years of age. Women who use oral contraceptives should be strongly advised not to smoke.

OCELLA contains 3 mg of the progestin drospirenone that has antimineralocorticoid activity, including the potential for hyperkalemia in high-risk patients, comparable to a 25 mg dose of spironolactone. OCELLA should not be used in patients with conditions that predispose to hyperkalemia (i.e. renal insufficiency, hepatic dysfunction and adrenal insufficiency). Women receiving daily, long-term treatment for chronic conditions or diseases with medications that may increase serum potassium, should have their serum potassium level checked during the first treatment cycle. Drugs that may increase serum potassium include ACE inhibitors, angiotensin–II receptor antagonists, potassium-sparing diuretics, heparin, aldosterone antagonists, and NSAIDs.

The use of oral contraceptives is associated with increased risks of several serious conditions including myocardial infarction, thromboembolism, stroke, hepatic neoplasia, gallbladder disease, and hypertension, although the risk of serious morbidity or mortality is very small in healthy women without underlying risk factors. The risk of morbidity and mortality increases significantly in the presence of other underlying risk factors such as hypertension, hyperlipidemias, obesity and diabetes.

Practitioners prescribing oral contraceptives should be familiar with the following information relating to these risks.

The information contained in this package insert is based principally on studies carried out in patients who used oral contraceptives with higher formulations of estrogens and progestogens than those in common use today. The effect of long-term use of the oral contraceptives with lower formulations of both estrogens and progestogens remains to be determined.

Throughout this labeling, epidemiologic studies reported are of two types: retrospective or case control studies and prospective or cohort studies. Case control studies provide a measure of the relative risk of a disease, namely, a ratio of the incidence of a disease among oral contraceptive users to that among nonusers. The relative risk does not provide information on the actual clinical occurrence of a disease. Cohort studies provide a measure of attributable risk, which is the difference in the incidence of disease between oral contraceptive users and nonusers. The attributable risk does provide information about the actual occurrence of a disease in the population. For further information, the reader is referred to a text on epidemiologic methods.

1. THROMBOEMBOLIC DISORDERS AND OTHER VASCULAR PROBLEMS

a. Myocardial infarction

An increased risk of myocardial infarction has been attributed to oral contraceptive use. This risk is primarily in smokers or women with other underlying risk factors for coronary- artery disease such as hypertension, hypercholesterolemia, morbid obesity, and diabetes. The relative risk of heart attack for current oral contraceptive users has been estimated to be two to six. The risk is very low under the age of 30.

Smoking in combination with oral contraceptive use has been shown to contribute substantially to the incidence of myocardial infarctions in women in their mid-thirties or older with smoking accounting for the majority of excess cases. Mortality rates associated with circulatory disease have been shown to increase substantially in smokers over the age of 35 and nonsmokers over the age of 40 (Table III) among women who use oral contraceptives.

TABLE III. CIRCULATORY DISEASE MORTALITY RATES PER 100,000 WOMAN-YEARS BY AGE SMOKING STATUS AND ORAL CONTRACEPTIVE USE
AGE | EVER-USERS NON-SMOKERS | EVER-USERS SMOKERS | CONTROL NON-SMOKERS | CONTROL SMOKERS
15–24 | 0 | 10.5 | 0 | 0
25–34 | 4.4 | 14.2 | 2.7 | 4.2
35–44 | 21.5 | 63.4 | 6.4 | 15.2
45+ | 52.4 | 206.7 | 11.4 | 27.9
(Adapted from P.M. Layde and V. Beral)

Oral contraceptives may compound the effects of well-known risk factors, such as hypertension, diabetes, hyperlipidemias, age and obesity. In particular, some progestogens are known to decrease HDL cholesterol and cause glucose intolerance, while estrogens may create a state of hyperinsulinism. Oral contraceptives have been shown to increase blood pressure among users (see section 9 in WARNINGS). Similar effects on risk factors have been associated with an increased risk of heart disease. Oral contraceptives must be used with caution in women with cardiovascular disease risk factors.

b. Thromboembolism

An increased risk of thromboembolic and thrombotic disease associated with the use of oral contraceptives is well established. Case control studies have found the relative risk of users compared to nonusers to be 3 for the first episode of superficial venous thrombosis, 4 to 11 for deep vein thrombosis or pulmonary embolism, and 1.5 to 6 for women with predisposing conditions for venous thromboembolic disease. Cohort studies have shown the relative risk to be somewhat lower, about 3 for new cases and about 4.5 for new cases requiring hospitalization. The risk of thromboembolic disease due to oral contraceptives is not related to length of use and disappears after pill use is stopped.

A two- to four-fold increase in the relative risk of post-operative thromboembolic complications has been reported with the use of oral contraceptives. The relative risk of venous thrombosis in women who have predisposing conditions is twice that of women without such medical conditions. If feasible, oral contraceptives should be discontinued from at least four weeks prior to and for two weeks after elective surgery of a type associated with an increase in risk of thromboembolism and during and following prolonged immobilization. Since the immediate postpartum period is also associated with an increased risk of thromboembolism, oral contraceptives should be started no earlier than four to six weeks after delivery.

Several studies have investigated the relative risks of thromboembolism in women using OCELLA compared to those in women using COCs containing other progestins. Two prospective cohort studies, both evaluating the risk of venous and arterial thromboembolism and death, were initiated at the time of OCELLA approval.^1,^2 The first (EURAS) showed the risk of thromboembolism (particularly venous thromboembolism) and death in OCELLA users to be comparable to that of other oral contraceptive preparations, including those containing levonorgestrel (a so-called second generation COC). The second prospective cohort study (Ingenix) also showed a comparable risk of thromboembolism in OCELLA users compared to users of other COCs, including those containing levonorgestrel. In the second study, COC comparator groups were selected based on their having similar characteristics to those being prescribed OCELLA.

Two additional epidemiological studies, one case-control study (van Hylckama Vlieg et al. ^3) and one retrospective cohort study (Lidegaard et al. ^4) suggested that the risk of venous thromboembolism occurring in OCELLA users was higher than that for users of levonorgestrel-containing COCs and lower than that for users of desogestrel/gestodene-containing COCs (so-called third generation COCs). In the case-control study, however, the number of OCELLA cases was very small (1.2% of all cases) making the risk estimates unreliable. The relative risk for OCELLA users in the retrospective cohort study was greater than that for users of other COC products when considering women who used the products for less than one year. However, these one-year estimates may not be reliable because the analysis may include women of varying risk levels. Among women who used the product for 1 to 4 years, the relative risk was similar for users of OCELLA to that for users of other COC products.

c. Cerebrovascular diseases

Oral contraceptives have been shown to increase both the relative and attributable risks of cerebrovascular events (thrombotic and hemorrhagic strokes), although, in general, the risk is greatest among older (>35 years), hypertensive women who also smoke. Hypertension was found to be a risk factor, for both users and nonusers, for both types of strokes, while smoking interacted to increase the risk for hemorrhagic strokes.

In a large study, the relative risk of thrombotic strokes has been shown to range from 3 for normotensive users to 14 for users with severe hypertension. The relative risk of hemorrhagic stroke is reported to be 1.2 for nonsmokers who used oral contraceptives, 2.6 for smokers who did not use oral contraceptives, 7.6 for smokers who used oral contraceptives, 1.8 for normotensive users and 25.7 for users with severe hypertension. The attributable risk is also greater in older women.

d. Dose-related risk of vascular disease from oral contraceptives

A positive association has been observed between the amount of estrogen and progestogen in oral contraceptives and the risk of vascular disease. A decline in serum high-density lipoproteins (HDL) has been reported with many progestational agents. A decline in serum high-density lipoproteins has been associated with an increased incidence of ischemic heart disease. Because estrogens increase HDL cholesterol, the net effect of an oral contraceptive depends on a balance achieved between doses of estrogen and progestogen and the nature and absolute amount of progestogen used in the contraceptive. The amount of both hormones should be considered in the choice of an oral contraceptive.

Minimizing exposure to estrogen and progestogen is in keeping with good principles of therapeutics. For any particular estrogen/progestogen combination, the dosage regimen prescribed should be one which contains the least amount of estrogen and progestogen that is compatible with a low failure rate and the needs of the individual patient. New acceptors of oral contraceptive agents should be started on preparations containing the lowest estrogen content which provides satisfactory results in the individual.

e. Persistence of risk of vascular disease

There are two studies which have shown persistence of risk of vascular disease for ever-users of oral contraceptives. In a study in the United States, the risk of developing myocardial infarction after discontinuing oral contraceptives persists for at least 9 years for women aged 40 to 49 years who had used oral contraceptives for five or more years, but this increased risk was not demonstrated in other age groups. In another study in Great Britain, the risk of developing cerebrovascular disease persisted for at least 6 years after discontinuation of oral contraceptives, although excess risk was very small. However, both studies were performed with oral contraceptive formulations containing 50 micrograms or higher of estrogens.

2. ESTIMATES OF MORTALITY FROM CONTRACEPTIVE USE

One study gathered data from a variety of sources which have estimated the mortality rate associated with different methods of contraception at different ages (Table IV). These estimates include the combined risk of death associated with contraceptive methods plus the risk attributable to pregnancy in the event of method failure. Each method of contraception has its specific benefits and risks. The study concluded that with the exception of oral contraceptive users 35 and older who smoke and 40 and older who do not smoke, mortality associated with all methods of birth control is below that associated with childbirth.

The observation of a possible increase in risk of mortality with age for oral contraceptive users is based on data gathered in the 1970's — but not reported until 1983. However, current clinical practice involves the use of lower estrogen dose formulations combined with careful restriction of oral contraceptive use to women who do not have the various risk factors listed in this labeling.

Because of these changes in practice and, also, because of some limited new data which suggest that the risk of cardiovascular disease with the use of oral contraceptives may now be less than previously observed, the Fertility and Maternal Health Drugs Advisory Committee was asked to review the topic in 1989. The Committee concluded that although cardiovascular disease risks may be increased with oral contraceptive use after age 40 in healthy nonsmoking women (even with the newer low-dose formulations), there are greater potential health risks associated with pregnancy in older women and with the alternative surgical and medical procedures which may be necessary if such women do not have access to effective and acceptable means of contraception.

Therefore, the Committee recommended that the benefits of oral contraceptive use by healthy nonsmoking women over 40 may outweigh the possible risks. Of course, women of all ages who take oral contraceptives, should take the lowest possible dose formulation that is effective.

TABLE IV ANNUAL NUMBER OF BIRTH-RELATED OR METHOD-RELATED DEATHS ASSOCIATED WITH CONTROL OF FERTILITY PER 100,000 NONSTERILE WOMEN, BY FERTILITY-CONTROL METHOD ACCORDING TO AGE
Method of Control and Outcome | 15–19 | 20–24 | 25–29 | 30–34 | 35–39 | 40–44
No fertility control methods [Deaths are birth-related] | 7 | 7.4 | 9.1 | 14.8 | 25.7 | 28.2
Oral contraceptives nonsmoker [Deaths are method-related] | 0.3 | 0.5 | 0.9 | 1.9 | 13.8 | 31.6
Oral contraceptives smoker | 2.2 | 3.4 | 6.6 | 13.5 | 51.1 | 117.2
lUD | 0.8 | 0.8 | 1 | 1 | 1.4 | 1.4
Condom | 1.1 | 1.6 | 0.7 | 0.2 | 0.3 | 0.4
Diaphragm/spermicide | 1.9 | 1.2 | 1.2 | 1.3 | 2.2 | 2.8
Periodic abstinence | 2.5 | 1.6 | 1.6 | 1.7 | 2.9 | 3.6
Adapted from H.W. Ory, Family Planning Perspectives, 15:57-63, 1983.

3. CARCINOMA OF THE REPRODUCTIVE ORGANS AND BREASTS

Numerous epidemiological studies have been performed on the incidence of breast, endometrial, ovarian and cervical cancer in women using oral contraceptives.

The risk of having breast cancer diagnosed may be slightly increased among current and recent users of COCs. However, this excess risk appears to decrease over time after COC discontinuation and by 10 years after cessation the increased risk disappears. The risk does not appear to increase with duration of use and no consistent relationships have been found with dose or type of steroid. Most studies show a similar pattern of risk with COC use regardless of a woman's reproductive history or her family breast cancer history. Some studies have found a small increase in risk for women who first use COCs before age 20.

Breast cancers diagnosed in current or previous OC users tend to be less clinically advanced than in nonusers.

Women who currently have or have had breast cancer should not use oral contraceptives because breast cancer is a hormonally-sensitive tumor.

Some studies suggest that oral contraceptive use has been associated with an increase in the risk of cervical intraepithelial neoplasia in some populations of women. However, there continues to be controversy about the extent to which such findings may be due to differences in sexual behavior and other factors.

In spite of many studies of the relationship between oral contraceptive use and breast and cervical cancers, a cause-and-effect relationship has not been established.

4. HEPATIC NEOPLASIA

Benign hepatic adenomas are associated with oral contraceptive use, although the incidence of benign tumors is rare in the United States. Indirect calculations have estimated the attributable risk to be in the range of 3.3 cases/100,000 for users, a risk that increases after four or more years of use. Rupture of rare, benign, hepatic adenomas may cause death through intra-abdominal hemorrhage.

Studies from Britain have shown an increased risk of developing hepatocellular carcinoma in long-term (>8 years) oral contraceptive users. However, these cancers are extremely rare in the U.S. and the attributable risk (the excess incidence) of liver cancers in oral contraceptive users approaches less than one per million users.

5. OCULAR LESIONS

There have been clinical case reports of retinal thrombosis associated with the use of oral contraceptives. Oral contraceptives should be discontinued if there is unexplained partial or complete loss of vision; onset of proptosis or diplopia; papilledema; or retinal vascular lesions. Appropriate diagnostic and therapeutic measures should be undertaken immediately.

6. ORAL CONTRACEPTIVE USE BEFORE OR DURING EARLY PREGNANCY

Extensive epidemiological studies have revealed no increased risk of birth defects in women who have used oral contraceptives prior to pregnancy. Studies also do not suggest a teratogenic effect, particularly in so far as cardiac anomalies and limb-reduction defects are concerned, when taken inadvertently during early pregnancy.

The administration of oral contraceptives to induce withdrawal bleeding should not be used as a test for pregnancy. Oral contraceptives should not be used during pregnancy to treat threatened or habitual abortion.

It is recommended that for any patient who has missed two consecutive periods, pregnancy should be ruled out. If the patient has not adhered to the prescribed dosing schedule, the possibility of pregnancy should be considered at the time of the first missed period. Oral contraceptive use should be discontinued if pregnancy is confirmed.

7. GALLBLADDER DISEASE

Earlier studies have reported an increased lifetime relative risk of gallbladder surgery in users of oral contraceptives and estrogens. More recent studies, however, have shown that the relative risk of developing gallbladder disease among oral contraceptive users may be minimal. The recent findings of minimal risk may be related to the use of oral contraceptive formulations containing lower hormonal doses of estrogens and progestogens.

8. CARBOHYDRATE AND LIPID METABOLIC EFFECTS

Oral contraceptives have been shown to cause glucose intolerance in a significant percentage of users. Oral contraceptives containing greater than 75 micrograms of estrogens cause hyperinsulinism, while lower doses of estrogen cause less glucose intolerance. Progestogens increase insulin secretion and create insulin resistance, this effect varying with different progestational agents. However, in the nondiabetic woman, oral contraceptives appear to have no effect on fasting blood glucose. Because of these demonstrated effects, prediabetic and diabetic women should be carefully observed while taking oral contraceptives.

A small proportion of women will have persistent hypertriglyceridemia while on the pill. As discussed earlier (see WARNINGS, 1a and 1d), changes in serum triglycerides and lipoprotein levels have been reported in oral contraceptive users.

9. ELEVATED BLOOD PRESSURE

An increase in blood pressure has been reported in women taking oral contraceptives and this increase is more likely in older oral contraceptive users and with continued use. Data from the Royal College of General Practitioners and subsequent randomized trials have shown that the incidence of hypertension increases with increasing concentrations of progestogens.

Women with a history of hypertension or hypertension-related diseases, or renal disease should be encouraged to use another method of contraception. If women with hypertension elect to use oral contraceptives, they should be monitored closely, and if significant elevation of blood pressure occurs, oral contraceptives should be discontinued. For most women, elevated blood pressure will return to normal after stopping oral contraceptives and there is no difference in the occurrence of hypertension among ever- and never-users.

10. HEADACHE

The onset or exacerbation of migraine or development of headache with a new pattern which is recurrent, persistent or severe requires discontinuation of oral contraceptives and evaluation of the cause.

11. BLEEDING IRREGULARITIES

Breakthrough bleeding and spotting are sometimes encountered in patients on oral contraceptives, especially during the first three months of use. Nonhormonal causes should be considered and adequate diagnostic measures taken to rule out malignancy or pregnancy in the event of breakthrough bleeding, as in the case of any abnormal vaginal bleeding. If pathology has been excluded, time or a change to another formulation may solve the problem. In the event of amenorrhea, pregnancy should be ruled out.

Some women may encounter post-pill amenorrhea or oligomenorrhea, especially when such a condition was pre-existent.

PRECAUTIONS

1. GENERAL

Patients should be counseled that this product does not protect against HIV infection (AIDS) and other sexually transmitted diseases.

2. PHYSICAL EXAMINATION AND FOLLOW-UP

It is good medical practice for all women to have annual history and physical examinations, including women using oral contraceptives. The physical examination, however, may be deferred until after initiation of oral contraceptives if requested by the woman and judged appropriate by the clinician. The physical examination should include special reference to blood pressure, breasts, abdomen and pelvic organs, including cervical cytology and relevant laboratory tests. In case of undiagnosed, persistent or recurrent abnormal vaginal bleeding, appropriate measures should be conducted to rule out malignancy. Women with a strong family history of breast cancer or who have breast nodules should be monitored with particular care.

3. LIPID DISORDERS

Women who are being treated for hyperlipidemias should be followed closely if they elect to use oral contraceptives. Some progestogens may elevate LDL levels and may render the control of hyperlipidemias more difficult.

4. LIVER FUNCTION

If jaundice develops in any woman receiving oral contraceptives, the medication should be discontinued. Steroid hormones may be poorly metabolized in patients with impaired liver function.

5. FLUID RETENTION

Oral contraceptives may cause some degree of fluid retention. They should be prescribed with caution, and only with careful monitoring, in patients with conditions which might be aggravated by fluid retention.

6. EMOTIONAL DISORDERS

Women with a history of depression should be carefully observed and the drug discontinued if depression recurs to a serious degree.

7. CONTACT LENSES

Contact-lens wearers who develop visual changes or changes in lens tolerance should be assessed by an ophthalmologist.

8. DRUG INTERACTIONS

Effects of Other Drugs on Combined Hormonal Contraceptives

Rifampin

Metabolism of ethinyl estradiol and some progestins (e.g., norethindrone) is increased by rifampin. A reduction in contraceptive effectiveness and an increase in menstrual irregularities have been associated with concomitant use of rifampin.

Anticonvulsants

Anticonvulsants such as phenobarbital, phenytoin, and carbamazepine have been shown to increase the metabolism of ethinyl estradiol and/or some progestins, which could result in a reduction of contraceptive effectiveness.

Antibiotics

Pregnancy while taking combined hormonal contraceptives has been reported when the combined hormonal contraceptives were administered with antimicrobials such as ampicillin, tetracycline, and griseofulvin. However, clinical pharmacokinetic studies have not demonstrated any consistent effects of antibiotics (other than rifampin) on plasma concentrations of synthetic steroids.

Atorvastatin

Coadministration of atorvastatin and an oral contraceptive increased AUC values for norethindrone and ethinyl estradiol by approximately 30% and 20%, respectively.

St. John's Wort

Herbal products containing St. John's Wort (hypericum perforatum) may induce hepatic enzymes (cytochrome P450) and p-glycoprotein transporter and may reduce the effectiveness of oral contraceptives and emergency contraceptive pills. This may also result in breakthrough bleeding.

Other

Ascorbic acid and acetaminophen may increase plasma concentrations of some synthetic estrogens, possibly by inhibition of conjugation. A reduction in contraceptive effectiveness and an increased incidence of menstrual irregularities has been suggested with phenylbutazone.

Effects of Drospirenone on Other Drugs

Metabolic Interactions

Metabolism of DRSP and potential effects of DRSP on hepatic cytochrome P450 (CYP) enzymes have been investigated in in vitro and in vivo studies (see Metabolism). In in vitro studies DRSP did not affect turnover of model substrates of CYP1A2 and CYP2D6, but had an inhibitory influence on the turnover of model substrates of CYP1A1, CYP2C9, CYP2C19 and CYP3A4 with CYP2C19 being the most sensitive enzyme.

The potential effect of DRSP on CYP2C19 activity was investigated in a clinical pharmacokinetic study using omeprazole as a marker substrate. In the study with 24 postmenopausal women [including 12 women with homozygous (wild type) CYP2C19 genotype and 12 women with heterozygous CYP2C19 genotype] the daily oral administration of 3 mg DRSP for 14 days did not affect the oral clearance of omeprazole (40 mg, single oral dose). Based on the available results of in vivo and in vitro studies it can be concluded that, at clinical dose level, DRSP shows little propensity to interact to a significant extent with cytochrome P450 enzymes.

Interactions With Drugs That Have The Potential To Increase Serum Potassium

There is a potential for an increase in serum potassium in women taking OCELLA with other drugs (see BOLDED WARNINGS). Of note, occasional or chronic use of NSAID medication was not restricted in any of the OCELLA clinical trials.

A drug-drug interaction study of DRSP 3 mg/estradiol (E2) 1 mg versus placebo was performed in 24 mildly hypertensive postmenopausal women taking enalapril maleate 10 mg twice daily. Potassium levels were obtained every other day for a total of 2 weeks in all subjects. Mean serum potassium levels in the DRSP/E2 treatment group relative to baseline were 0.22 mEq/L higher than those in the placebo group. Serum potassium concentrations also were measured at multiple timepoints over 24 hours at baseline and on Day 14. On Day 14, the ratios for serum potassium Cmax and AUC in the DRSP/E2 group to those in the placebo group were 0.955 (90% CI: 0.914, 0.999) and 1.01 (90% CI: 0.944, 1.08), respectively. No patient in either treatment group developed hyperkalemia (serum potassium concentrations > 5.5 mEq/L).

Effects of Combined Hormonal Contraceptives on Other Drugs

Combined oral contraceptives containing ethinyl estradiol may inhibit the metabolism of other compounds. Increased plasma concentrations of cyclosporine, prednisolone, and theophylline have been reported with concomitant administration of oral contraceptives. In addition, oral contraceptives may induce the conjugation of other compounds. Decreased plasma concentrations of acetaminophen and increased clearance on temazepam, salicylic acid, morphine, and clofibric acid have been noted when these drugs were administered with oral contraceptives.

9. INTERACTIONS WITH LABORATORY TESTS

Certain endocrine- and liver-function tests and blood components may be affected by oral contraceptives:

a. Increased prothrombin and factors VII, VIII, IX and X; decreased antithrombin 3; increased norepinephrine-induced platelet aggregability.

b. Increased thyroid-binding globulin (TBG) leading to increased circulating total thyroid hormone, as measured by protein-bound iodine (PBI), T4 by column or by radioimmunoassay. Free T3 resin uptake is decreased, reflecting the elevated TBG, free T4 concentration is unaltered.

c. Other binding proteins may be elevated in serum.

d. Sex-hormone-binding globulins are increased and result in elevated levels of total circulating sex steroids and corticoids; however, free or biologically active levels remain unchanged.

e. Triglycerides may be increased.

f. Glucose tolerance may be decreased.

g. Serum folate levels may be depressed by oral contraceptive therapy. This may be of clinical significance if a woman becomes pregnant shortly after discontinuing oral contraceptives.

10. CARCINOGENESIS, MUTAGENESIS, IMPAIRMENT OF FERTILITY

In a 24 month oral carcinogenicity study in mice dosed with 10 mg/kg/day drospirenone alone or 1 + 0.01, 3 + 0.03 and 10 + 0.1 mg/kg/day of drospirenone and ethinyl estradiol, 0.1 to 2 times the exposure (AUC of drospirenone) of women taking a contraceptive dose, there was an increase in carcinomas of the harderian gland in the group that received the high dose of drospirenone alone. In a similar study in rats given 10 mg/kg/day drospirenone alone or 0.3 + 0.003, 3 + 0.03 and 10 + 0.1 mg/kg/day drospirenone and ethinyl estradiol, 0.8 to 10 times the exposure of women taking a contraceptive dose, there was an increased incidence of benign and total (benign and malignant) adrenal gland pheochromocytomas in the group receiving the high dose of drospirenone. Drospirenone was not mutagenic in a number of in vitro (Ames, Chinese Hamster Lung gene mutation and chromosomal damage in human lymphocytes) and in vivo (mouse micronucleus) genotoxicity tests. Drospirenone increased unscheduled DNA synthesis in rat hepatocytes and formed adducts with rodent liver DNA but not with human liver DNA. See WARNINGS.

11. PREGNANCY

Pregnancy category X. See CONTRAINDICATIONS and WARNINGS.

Estrogens and progestins should not be used during pregnancy. Fourteen pregnancies that occurred with OCELLA exposure in utero (none with more than a single cycle of exposure) have been identified. One infant was born with esophageal atresia. A causal association with OCELLA is unknown.

A teratology study in pregnant rats given drospirenone orally at doses of 5, 15 and 45 mg/kg/day, 6 to 50 times the human exposure based on AUC of drospirenone, resulted in an increased number of fetuses with delayed ossification of bones of the feet in the two higher doses. A similar study in rabbits dosed orally with 1, 30 and 100 mg/kg/day drospirenone, 2 to 27 times the human exposure, resulted in an increase in fetal loss and retardation of fetal development (delayed ossification of small bones, multiple fusions of ribs) at the high dose only. When drospirenone was administered with ethinyl estradiol (100:1) during late pregnancy (the period of genital development) at doses of 5, 15 and 45 mg/kg, there was a dose dependent increase in feminization of male rat fetuses. In a study in 36 cynomolgous monkeys, no teratogenic or feminization effects were observed with orally administered drospirenone and ethinyl estradiol (100:1) at doses up to 10 mg/kg/day drospirenone, 30 times the human exposure.

12. NURSING MOTHERS

Small amounts of oral contraceptive steroids have been identified in the milk of nursing mothers, and a few adverse effects on the child have been reported, including jaundice and breast enlargement. In addition, oral contraceptives given in the postpartum period may interfere with lactation by decreasing the quantity and quality of breast milk. If possible, the nursing mother should be advised not to use oral contraceptives but to use other forms of contraception until she has completely weaned her child.

After oral administration of OCELLA about 0.02% of the drospirenone dose was excreted into the breast milk of postpartum women within 24 hours. This results in a maximal daily dose of about 3 mcg drospirenone in an infant.

13. PEDIATRIC USAGE

Safety and efficacy of OCELLA have been established in women of reproductive age. Safety and efficacy are expected to be the same for postpubertal adolescents under the age of 16 and for users 16 years and older. Use of this product before menarche is not indicated.

INFORMATION FOR THE PATIENT

See Patient Labeling printed below.

ADVERSE REACTIONS

An increased risk of the following serious adverse reactions has been associated with the use of oral contraceptives (see WARNINGS).

- Thrombophlebitis
- Arterial thromboembolism
- Pulmonary embolism
- Myocardial infarction
- Cerebral hemorrhage
- Cerebral thrombosis
- Hypertension
- Gallbladder disease
- Hepatic adenomas or benign liver tumors

There is evidence of an association between the following conditions and the use of oral contraceptives, although additional confirmatory studies are needed:

- Mesenteric thrombosis
- Retinal thrombosis

The following adverse reactions have been reported in patients receiving oral contraceptives and are believed to be drug-related:

- Nausea
- Vomiting
- Gastrointestinal symptoms (such as abdominal cramps and bloating)
- Breakthrough bleeding
- Spotting
- Change in menstrual flow
- Amenorrhea
- Temporary infertility after discontinuation of treatment
- Edema
- Melasma which may persist
- Breast changes: tenderness, enlargement, secretion
- Change in weight (increase or decrease)
- Change in cervical erosion and secretion
- Diminution in lactation when given immediately postpartum
- Cholestatic jaundice
- Migraine
- Rash (allergic)
- Mental depression
- Reduced tolerance to carbohydrates
- Vaginal candidiasis
- Change in corneal curvature (steepening)
- lntolerance to contact lenses

The following adverse reactions have been reported in users of oral contraceptives and a causal association has been neither confirmed nor refuted:

- Acne
- Budd-Chiari syndrome
- Cataracts
- Changes in appetite
- Changes in libido
- Colitis
- Cystitis-like syndrome
- Dizziness
- Erythema multiforme
- Erythema nodosum
- Headache
- Hemolytic uremic syndrome
- Hemorrhagic eruption
- Hirsutism
- Impaired renal function
- Loss of scalp hair
- Nervousness
- Porphyria
- Pre-menstrual syndrome
- Vaginitis

The following are the most common adverse events reported with use of OCELLA during the clinical trials, occurring in > 1% of subjects and which may or may not be drug related: Headache, Menstrual Disorder, Breast Pain, Abdominal Pain, Nausea, Leukorrhea, Flu Syndrome, Acne, Vaginal Moniliasis, Depression, Diarrhea, Asthenia, Dysmenorrhea, Back Pain, Infection, Pharyngitis, Intermenstrual Bleeding, Migraine, Vomiting, Dizziness, Nervousness, Vaginitis, Sinusitis, Cystitis, Bronchitis, Gastroenteritis, Allergic Reaction, Urinary Tract Infection, Pruritus, Emotional Lability, Surgery, Rash, Upper Respiratory Infection.

OVERDOSAGE

Serious ill effects have not been reported following acute ingestion of large doses of other oral contraceptives by young children. Overdosage may cause nausea, and withdrawal bleeding may occur in females. Drospirenone, however, is a spironolactone analogue which has antimineralocorticoid properties. Serum concentration of potassium and sodium, and evidence of metabolic acidosis, should be monitored in cases of overdose.

NON-CONTRACEPTIVE HEALTH BENEFITS

The following non-contraceptive health benefits related to the use of oral contraceptives are supported by epidemiological studies which largely utilized oral contraceptive formulations containing doses exceeding 0.035 mg of ethinyl estradiol or 0.05 mg mestranol.

Effects on menses

- increased menstrual cycle regularity
- decreased blood loss and decreased incidence of iron-deficiency anemia
- decreased incidence of dysmenorrhea

Effects related to inhibition of ovulation

- decreased incidence of functional ovarian cysts
- decreased incidence of ectopic pregnancies

Effects from long-term use

- decreased incidence of fibroadenomas and fibrocystic disease of the breast
- decreased incidence of acute pelvic inflammatory disease
- decreased incidence of endometrial cancer
- decreased incidence of ovarian cancer

DOSAGE AND ADMINISTRATION

OCELLA

To achieve maximum contraceptive effectiveness, OCELLA (drospirenone and ethinyl estradiol) must be taken exactly as directed at intervals not exceeding 24 hours.

OCELLA consists of 21 tablets of a monophasic combined hormonal preparation plus 7 inert tablets. The dosage of OCELLA is one yellow tablet daily for 21 consecutive days followed by 7 white inert tablets per menstrual cycle. A patient should begin to take OCELLA either on the first day of her menstrual period (Day 1 Start) or on the first Sunday after the onset of her menstrual period (Sunday Start).

Day 1 Start. During the first cycle of OCELLA use, the patient should be instructed to take one yellow OCELLA daily, beginning on day one (1) of her menstrual cycle. (The first day of menstruation is day one.) She should take one yellow OCELLA daily for 21 consecutive days, followed by one white inert tablet daily on menstrual cycle days 22 through 28. It is recommended that OCELLA be taken at the same time each day, preferably after the evening meal or at bedtime. If OCELLA is first taken later than the first day of the menstrual cycle, OCELLA should not be considered effective as a contraceptive until after the first 7 consecutive days of product administration. The possibility of ovulation and conception prior to initiation of medication should be considered.

Sunday Start. During the first cycle of OCELLA use, the patient should be instructed to take one yellow OCELLA daily, beginning on the first Sunday after the onset of her menstrual period. She should take one yellow OCELLA daily for 21 consecutive days, followed by one white inert tablet daily on menstrual cycle days 22 through 28. It is recommended that OCELLA be taken at the same time each day, preferably after the evening meal or at bedtime. OCELLA should not be considered effective as a contraceptive until after the first 7 consecutive days of product administration. The possibility of ovulation and conception prior to initiation of medication should be considered.

The patient should begin her next and all subsequent 28-day regimens of OCELLA on the same day of the week that she began her first regimen, following the same schedule. She should begin taking her yellow tablets on the next day after ingestion of the last white tablet, regardless of whether or not a menstrual period has occurred or is still in progress. Anytime a subsequent cycle of OCELLA is started later than the day following administration of the last white tablet, the patient should use another method of contraception until she has taken a yellow OCELLA daily for seven consecutive days.

When switching from another oral contraceptive, OCELLA should be started on the same day that a new pack of the previous oral contraceptive would have been started.

Withdrawal bleeding usually occurs within 3 days following the last yellow tablet. If spotting or breakthrough bleeding occurs while taking OCELLA, the patient should be instructed to continue taking her OCELLA as instructed and by the regimen described above. She should be instructed that this type of bleeding is usually transient and without significance; however, if the bleeding is persistent or prolonged, the patient should be advised to consult her physician.

Although the occurrence of pregnancy is unlikely if OCELLA is taken according to directions, if withdrawal bleeding does not occur, the possibility of pregnancy must be considered. If the patient has not adhered to the prescribed dosing schedule (missed one or more active tablets or started taking them on a day later than she should have), the possibility of pregnancy should be considered at the time of the first missed period and appropriate diagnostic measures taken. If the patient has adhered to the prescribed regimen and misses two consecutive periods, pregnancy should be ruled out. Hormonal contraception should be discontinued if pregnancy is confirmed.

The risk of pregnancy increases with each active yellow tablet missed. For additional patient instructions regarding missed pills, see the "WHAT TO DO IF YOU MISS PILLS" section in the DETAILED PATIENT LABELING which follows. If breakthrough bleeding occurs following missed tablets, it will usually be transient and of no consequence. If the patient misses one or more white tablets, she should still be protected against pregnancy provided she begins taking yellow tablets again on the proper day.

In the nonlactating mother, OCELLA may be initiated 4 weeks postpartum, for contraception. When the tablets are administered in the postpartum period, the increased risk of thromboembolic disease associated with the postpartum period must be considered. (See CONTRAINDICATIONS, WARNINGS, and PRECAUTIONS concerning thromboembolic disease.)

HOW SUPPLIED

OCELLA Tablets (drospirenone and ethinyl estradiol) are available in 28 tablets (BLISTER pack) (NDC 54868-5922-0).

Each pack contains 21 active yellow round, unscored, film coated tablets each containing 3 mg drospirenone and 0.03 mg ethinyl estradiol, and 7 inert white round, unscored, film coated tablets.

Store at 25° C (77°F); excursions permitted to 15–30°C (59–86°F). [See USP Controlled Room Temperature.]

REFERENCES

1. Dinger JC, Heinemann LAJ, et al: The safety of a drospirenone-containing oral contraceptive: final results from the European active surveillance study on oral contraceptives based on 142,475 women-years of observation. Contraception 2007;75:344-354.

2. Seeger JD, Loughlin J, Eng PM, et al: Risk of thromboembolism in women taking ethinylestradiol/drospirenone and other oral contraceptives. Obstetrics & Gynecology 2007;110(3):587-593.

3. van Hylckama Vlieg A, Helmerhorst FM, Vandenbroucke JP, et al: The venous thrombotic risk of oral contraceptives, effects of oestrogen dose and progestogen type: results of the MEGA case-control study. BMJ 2009;339:b2921.

4. Lidegaard O, Lokkegaard E, Svendsen AL, et al: Hormonal contraception and risk of venous thromboembolism: national follow-up study. BMJ 2009; 339:b2890.

Manufactured by:

Bayer HealthCare Pharmaceuticals Inc.

Manufactured in: Germany

Relabeling of "Additional" label by:
Physicians Total Care, Inc.
Tulsa, OK 74146

BRIEF SUMMARY PATIENT PACKAGE INSERT

OCELLA ® 28 Tablets

(drospirenone and ethinyl estradiol)

28 tablets containing the following:

21 yellow — "active" tablets

7 whit — "inert" tablets

This product (like all oral contraceptives) is intended to prevent pregnancy. It does not protect against HIV infection (AIDS) and other sexually transmitted diseases.

OCELLA is different from other birth-control pills because it contains the progestin drospirenone. Drospirenone may increase potassium. Therefore, you should not take OCELLA if you have kidney, liver or adrenal disease because this could cause serious heart and health problems. Other drugs may also increase potassium. If you are currently on daily, long-term treatment for a chronic condition with any of the medications below, you should consult your healthcare provider about whether OCELLA is right for you, and during the first month that you take OCELLA, you should have a blood test to check your potassium level.

- NSAIDs (ibuprofen [Motrin®, Advil®], naproxen [Naprosyn®, Aleve® and others] when taken long-term and for treatment of arthritis or other problems)
- Potassium-sparing diuretics (spironolactone and others)
- Potassium supplementation
- ACE inhibitors (Capoten®, Vasotec®, Zestril® and others)
- Angiotensin-II receptor antagonists (Cozaar®, Diovan®, Avapro® and others)
- Heparin

Oral contraceptives, also known as "birth-control pills" or "the pill," are taken to prevent pregnancy, and when taken correctly, have a failure rate of less than 1% per year when used without missing any pills. The typical failure rate of large numbers of pill users is less than 5% per year when women who miss pills are included. However, forgetting to take pills considerably increases the chances of pregnancy.

For the majority of women, oral contraceptives can be taken safely. But there are some women who are at high risk of developing certain serious diseases that can be life–threatening or may cause temporary or permanent disability or death. The risks associated with taking oral contraceptives increase significantly if you:

- smoke
- have high blood pressure, diabetes, high cholesterol
- have or have had clotting disorders, heart attack, stroke, angina pectoris, cancer of the breast or sex organs, jaundice, or malignant or benign liver tumors.

You should not take the pill if you suspect you are pregnant or have unexplained vaginal bleeding.

BOXED WARNING

Cigarette smoking increases the risk of serious adverse effects on the heart and blood vessels from oral contraceptive use. This risk increases with age and with heavy smoking (15 or more cigarettes per day) and is quite marked in women over 35 years of age. Women who use oral contraceptives should not smoke.

Most side effects of the pill are not serious. The most common such effects are nausea, vomiting, bleeding between menstrual periods, weight gain, breast tenderness, and difficulty wearing contact lenses. These side effects, especially nausea and vomiting may subside within the first three months of use.

The serious side effects of the pill occur very infrequently, especially if you are in good health and are young. However, you should know that the following medical conditions have been associated with or made worse by the pill:

1. Blood clots in the legs (thrombophlebitis), lungs (pulmonary embolism), blockage or rupture of a blood vessel in the brain (stroke), blockage of blood vessels in the heart (heart attack and angina pectoris) or other organs of the body. As mentioned above, smoking increases the risk of heart attacks and strokes and subsequent serious medical consequences.

2. Liver tumors, which may rupture and cause severe bleeding. A possible but not definite association has been found with the pill and liver cancer. However, liver cancers are extremely rare. The chance of developing liver cancer from using the pill is thus even rarer.

3. High blood pressure, although blood pressure usually returns to normal when the pill is stopped.

4. Cancer of the breast. Various studies give conflicting reports on the relationship between breast cancer and oral contraceptive use. Oral contraceptive use may slightly increase your chance of having breast cancer diagnosed, particularly after using hormonal contraceptives at a younger age. After you stop using hormonal contraceptives, the chances of getting breast cancer begin to go back down. You should have regular breast examinations by a healthcare provider and examine your own breasts monthly. Tell your healthcare provider if you have a family history of breast cancer or if you have had breast nodules or an abnormal mammogram. Women who currently have or have had breast cancer should not use oral contraceptives because breast cancer is a hormone-sensitive tumor.

The symptoms associated with these serious side effects are discussed in the detailed leaflet given to you with your supply of pills. Notify your doctor or healthcare provider if you notice any unusual physical disturbances while taking the pill. ln addition, drugs such as rifampin, as well as some anticonvulsants, some antibiotics and some herbal products such as St. John's Wort, may decrease oral contraceptive effectiveness.

Taking the pill provides some important non-contraceptive benefits. These include less painful menstruation, less menstrual blood loss and anemia, fewer pelvic infections, and fewer cancers of the ovary and the lining of the uterus.

Be sure to discuss any medical condition you may have with your healthcare provider. Your healthcare provider will take a medical and family history before prescribing oral contraceptives and will examine you. The physical examination may be delayed to another time if you request it and the healthcare provider believes that it is appropriate to postpone it. You should be reexamined at least once a year while taking oral contraceptives. The detailed patient information booklet gives you further information which you should read and discuss with your healthcare provider.

This product (like all oral contraceptives) is intended to prevent pregnancy. It does not protect against transmission of HIV (AIDS) and other sexually transmitted diseases such as chlamydia, genital herpes, genital warts, gonorrhea, hepatitis B, and syphilis.

INSTRUCTIONS TO PATIENTS

HOW TO TAKE THE PILL

IMPORTANT POINTS TO REMEMBER

BEFORE YOU START TAKING YOUR PILLS

1. BE SURE TO READ THESE DIRECTIONS: Before you start taking your pills. Anytime you are not sure what to do.

2. THE RIGHT WAY TO TAKE THE PILL IS TO TAKE ONE PILL EVERY DAY AT THE SAME TIME.

If you miss pills you could get pregnant. This includes starting the pack late. The more pills you miss, the more likely you are to get pregnant.

3. MANY WOMEN HAVE SPOTTING OR LIGHT BLEEDING, OR MAY FEEL SICK TO THEIR STOMACH DURING THE FIRST 1–3 PACKS OF PILLS. If you do have spotting or light bleeding or feel sick to your stomach, do not stop taking the pill. The problem will usually go away. If it does not go away, check with your doctor or healthcare provider.

4. MISSING PILLS CAN ALSO CAUSE SPOTTING OR LIGHT BLEEDING, even when you make up these missed pills.

On the days you take two pills, to make up for missed pills, you could also feel a little sick to your stomach.

5. IF YOU HAVE VOMITING OR DIARRHEA, or IF YOU TAKE SOME MEDICINES, including some antibiotics and some herbal products such as St. John's Wort, your pills may not work as well.

Use a back-up method (such as condoms or spermicides) until you check with your doctor or healthcare provider.

6. IF YOU HAVE TROUBLE REMEMBERING TO TAKE THE PILL, talk to your doctor or healthcare provider about how to make pill-taking easier or about using another method of birth control.

7. IF YOU HAVE ANY QUESTIONS OR ARE UNSURE ABOUT THE INFORMATION IN THIS LEAFLET, call your doctor or healthcare provider.

BEFORE YOU START TAKING YOUR PILLS

1. DECIDE WHAT TIME OF DAY YOU WANT TO TAKE YOUR PILL.
It is important to take it at about the same time every day.

2. LOOK AT YOUR PILL PACK - IT HAS 28 PILLS:
The OCELLA pill pack has 21 yellow "active" pills (with hormones) to be taken for three weeks, followed by 7 white "reminder" pills (without hormones) to be taken for one week.

3. ALSO FIND:

1) where on the pack to start taking pills,

2) in what order to take the pills (follow the arrows)

3) the week numbers as shown in the diagram below

4. BE SURE YOU HAVE READY AT ALL TIMES:
ANOTHER KIND OF BIRTH CONTROL (such as condoms or spermicides) to use as a back-up in case you miss pills.

AN EXTRA, FULL PILL PACK.

WHEN TO START THE FIRST PACK OF PILLS

You have a choice for which day to start taking your first pack of pills. Decide with your doctor or healthcare provider which is the best day for you. Pick a time of day which will be easy to remember.

DAY 1 START:

1. Take the first yellow "active" pill of the first pack during the first 24 hours of your period.
2. You will not need to use a back-up method of birth control, since you are starting the pill at the beginning of your period.

SUNDAY START:

1. Take the first yellow "active" pill of the first pack on the Sunday after your period starts, even if you are still bleeding. If your period begins on Sunday, start the pack that same day.
2. Use another method of birth control (such as condoms or spermicides) as a back-up method if you have sex any time from the Sunday you start your first pack until the next Sunday (7 days).

WHAT TO DO DURING THE MONTH

1. TAKE ONE PILL AT THE SAME TIME EVERY DAY UNTIL THE PACK IS EMPTY

Do not skip pills even if you are spotting or bleeding between monthly periods or feel sick to your stomach (nausea).

Do not skip pills even if you do not have sex very often.

2. WHEN YOU FINISH A PACK OR SWITCH YOUR BRAND OF PILLS:

Start the next pack on the day after your last white "reminder" pill. Do not wait any days between packs.

WHAT TO DO IF YOU MISS PILLS

If you MISS 1 yellow "active" pill:

1. Take it as soon as you remember. Take the next pill at your regular time. This means you may take two pills in one day.
2. You do not need to use a back-up birth control method if you have sex.

If you MISS 2 yellow "active" pills in a row in WEEK 1 OR WEEK 2 of your pack:

1. Take two pills on the day you remember and two pills the next day.
2. Then take one pill a day until you finish the pack.
3. You MAY BECOME PREGNANT if you have sex in the 7 days after you miss pills. You MUST use another birth control method (such as condoms or spermicides) as a back-up for those 7 days.

If you MISS 2 yellow "active" pills in a row in the 3RD WEEK:

1. If you are a Day 1 Starter:

THROW OUT the rest of the pill pack and start a new pack that same day.

If you are a Sunday Starter:

Keep taking one pill every day until Sunday. On Sunday, THROW OUT the rest of the pack and start a new pack of pills that same day.

2. You may not have your period this month but this is expected. However, if you miss your period two months in a row, call your doctor or healthcare provider because you might be pregnant.

3. You MAY BECOME PREGNANT if you have sex in the 7 days after you miss pills. You MUST use another birth control method (such as condoms or spermicides) as a back-up for those 7 days.

If you MISS 3 OR MORE yellow "active" pills in a row (during the first 3 weeks).

1. If you are a Day 1 Starter:

THROW OUT the rest of the pill pack and start a new pack that same day.

If you are a Sunday Starter:

Keep taking 1 pill every day until Sunday. On Sunday, THROW OUT the rest of the pack and start a new pack of pills that same day.

2. You may not have your period this month but this is expected. However, if you miss your period two months in a row, call your doctor or healthcare provider because you might be pregnant.

3. You MAY BECOME PREGNANT if you have sex in the 7 days after you miss pills. You MUST use another birth control method (such as condoms or spermicides) as a back-up for those 7 days.

If you forget any of the 7 white "reminder" pills in Week 4:

THROW AWAY the pills you missed.

Keep taking one pill each day until the pack is empty.

You do not need a back-up method.

FINALLY, IF YOU ARE STILL NOT SURE WHAT TO DO ABOUT THE PILLS YOU HAVE MISSED:

Use a BACK-UP METHOD (such as condoms or spermicides) anytime you have sex.

KEEP TAKING ONE ACTIVE PILL EACH DAY until you can reach your doctor or healthcare provider.

For additional information see Detailed Patient Labeling

DETAILED PATIENT PACKAGE INSERT

This product (like all oral contraceptives) is intended to prevent pregnancy. It does not protect against HIV infection (AIDS) and other sexually transmitted diseases.

OCELLA is different from other birth-control pills because it contains the progestin drospirenone. Drospirenone may increase potassium. Therefore, you should not take OCELLA if you have kidney, liver or adrenal disease because this could cause serious heart and health problems. Other drugs may also increase potassium. If you are currently on daily, long-term treatment for a chronic condition with any of the medications below, you should consult your healthcare provider about whether OCELLA is right for you, and during the first month that you take OCELLA, you should have a blood test to check your potassium level.

- NSAIDs (ibuprofen [Motrin®, Advil®], naproxen [Naprosyn®, Aleve® and others] when taken long-term and for treatment of arthritis or other problems)
- Potassium-sparing diuretics (spironolactone and others)
- Potassium supplementation
- ACE inhibitors (Capoten®, Vasotec®, Zestril® and others)
- Angiotensin-II receptor antagonists (Cozaar®, Diovan®, Avapro® and others)
- Heparin

INTRODUCTION

Any woman who considers using oral contraceptives (the birth-control pill or "the pill") should understand the benefits and risks of using this form of birth control. This leaflet will give you much of the information you will need to make this decision and will also help you determine if you are at risk of developing any of the serious side effects of the pill. It will tell you how to use the pill properly so that it will be as effective as possible. However, this leaflet is not a replacement for a careful discussion between you and your healthcare provider. You should discuss the information provided in this leaflet with him or her, both when you first start taking the pill and during your revisits. You should also follow your healthcare provider's advice with regard to regular check-ups while you are on the pill.

EFFECTIVENESS OF ORAL CONTRACEPTIVES

Oral contraceptives or "birth-control pills" or "the pill" are used to prevent pregnancy and are more effective than other nonsurgical methods of birth control. When they are taken correctly, the chance of becoming pregnant is less than 1% (one pregnancy per 100 women per year of use) when used perfectly, without missing any pills. Typical failure rates, including women who don't always follow the instructions exactly, are about 5% per year. The chance of becoming pregnant increases with each missed pill during a menstrual cycle.

In comparison, typical failure rates for other nonsurgical methods of birth control during the first year of use are as follows:

Percentage of women experiencing an unintended pregnancy during the first year of typical use and first year of perfect use of contraception and the percentage continuing use at the end of the first year: United States.
 | % of Women Experiencing an; Accidental Pregnancy; Within the First Year of Use |  | % of Women; Continuing Use; At One Year
Method; (1) | Typical Use; (2) | Perfect Use; (3) | (4)
Chance | 85 | 85
Spermicides | 26 | 6 | 40
Periodic abstinence | 25 |  | 63
Calendar |  | 9
Ovulation method |  | 3
Sympto-thermal |  | 2
Post-ovulation |  | 1
Withdrawal | 19 | 4
Cap [With spermicidal cream or jelly.]
Parous women | 40 | 26 | 42
Nulliparous women | 20 | 9 | 56
Sponge
Parous women | 40 | 20 | 42
Nulliparous women | 20 | 9 | 56
Diaphragm | 20 | 6 | 56
Condom
Female (Reality) | 21 | 5 | 56
Male | 14 | 3 | 61
Pill | 5 |  | 71
progestin only |  | 0.5
combined |  | 0.1
IUD
Progesterone T: | 2 | 1.5 | 81
Copper T 380A | 0.8 | 0.6 | 78
Lng 20 | 0.1 | 0.1 | 81
Depo Provera | 0.3 | 0.3 | 70
Norplant and Norplant-2 | 0.05 | 0.05 | 88
Female Sterilization | 0.5 | 0.5 | 100
Male Sterilization | 0.15 | 0.1 | 100
Emergency Contraceptive Pills: Treatment initiated within 72 hours after unprotected intercourse reduces the risk of pregnancy by at least 75%
Lactational Amenorrhea Method: LAM is highly effective, temporary method of contraception
Source: Trussell J, Contraceptive efficacy. In Hatcher RA, Trussell J, Stewart F, Cates W, Stewart GK, Kowal D, Guest F, Contraceptive Technology: Seventeenth Revised Edition. New York NY: Irvington Publishers, 1998.

WHO SHOULD NOT TAKE ORAL CONTRACEPTIVES

Cigarette smoking increases the risk of serious adverse effects on the heart and blood vessels from oral contraceptive use. This risk increases with age and with heavy smoking (15 or more cigarettes per day) and is quite marked in women over 35 years of age. Women who use OCELLA should not smoke.

Some women should not use the pill. For example, you should not take OCELLA if you are pregnant or think you may be pregnant. You should also not use OCELLA if you have had any of the following conditions:

- A history of heart attack or stroke
- Blood clots in the legs (thrombophlebitis), lungs (pulmonary embolism), brain (stroke) or eyes
- A history of blood clots in the deep veins of your legs
- Chest pain (angina pectoris)
- Known or suspected breast cancer or cancer of the lining of the uterus, cervix or vagina
- Unexplained vaginal bleeding (until a diagnosis is reached by your doctor)
- Yellowing of the whites of the eyes or of the skin (jaundice) during pregnancy or during previous use of the pill
- Liver tumor (benign or cancerous)
- Known or suspected pregnancy

In addition, you should not use OCELLA if you have any of the following conditions:

- Kidney Disease
- Liver Disease
- Adrenal Disease

Tell your healthcare provider if you have ever had any of the above conditions (Your healthcare provider can recommend another method of birth control). If you are currently on daily, long-term treatment for a chronic condition with any of the following medications, you should consult your healthcare provider before taking OCELLA:

- NSAIDs (ibuprofen, naproxen and others)
- Potassium-sparing diuretics (spironolactone and others)
- Potassium supplementation
- ACE inhibitors (captopril, enalapril, lisinopril and others)
- Angiotensin-II receptor antagonists (Cozaar®, Diovan®, Avapro® and others)
- Heparin

OTHER CONSIDERATIONS BEFORE TAKING ORAL CONTRACEPTIVES

Tell your healthcare provider if you or any family member has ever had:

- Breast nodules, fibrocystic disease of the breast, an abnormal breast X-ray or mammogram
- Diabetes
- Elevated cholesterol or triglycerides
- High blood pressure
- Migraine or other headaches or epilepsy
- Mental depression
- Gallbladder, heart or kidney disease
- History of scanty or irregular menstrual periods

Women with any of these conditions should be checked often by their healthcare provider if they choose to use oral contraceptives.

Also, be sure to inform your doctor or healthcare provider if you smoke or take any medications.

RISKS OF TAKING ORAL CONTRACEPTIVES

1. RISK OF DEVELOPING BLOOD CLOTS

Blood clots and blockage of blood vessels are the most serious side effects of taking oral contraceptives and can be fatal. ln particular, a clot in the legs can cause thrombophlebitis and a clot that travels to the lungs can cause sudden blocking of the vessel carrying blood to the lungs. Rarely, clots occur in the blood vessels of the eye and may cause blindness, double vision, or impaired vision.

If you take oral contraceptives and need elective surgery, need to stay in bed for a prolonged illness or have recently delivered a baby, you may be at risk of developing blood clots. You should consult your doctor about stopping oral contraceptives three to four weeks before surgery and not taking oral contraceptives for two weeks after surgery or during bed rest. You should also not take oral contraceptives soon after delivery of a baby or a mid-trimester pregnancy loss or termination. It is advisable to wait for at least four weeks after delivery if you are not breast-feeding. If you are breast-feeding, you should wait until you have weaned your child before using the pill. (See also the section on breast-feeding in GENERAL PRECAUTIONS.)

2. HEART ATTACKS AND STROKES

Oral contraceptives may increase the tendency to develop strokes (stoppage or rupture of blood vessels in the brain) and angina pectoris and heart attacks (blockage of blood vessels in the heart). Any of these conditions can cause death or serious disability.

Smoking greatly increases the possibility of suffering heart attacks and strokes. Furthermore, smoking and the use of oral contraceptives greatly increase the chances of developing and dying of heart disease.

3. GALLBLADDER DISEASE

Oral contraceptive users probably have a greater risk than nonusers of having gallbladder disease, although this risk may be related to pills containing high doses of estrogens.

4. LIVER TUMORS

In rare cases, oral contraceptives can cause benign but dangerous liver tumors. These benign liver tumors can rupture and cause fatal internal bleeding. In addition, a possible but not definite association has been found with the pill and liver cancers in two studies, in which a few women who developed these very rare cancers were found to have used oral contraceptives for long periods. However, liver cancers are extremely rare. The chance of developing liver cancer from using the pill is thus even rarer.

5. CANCER OF THE REPRODUCTIVE ORGANS AND BREASTS

Various studies give conflicting reports on the relationship between breast cancer and oral contraceptive use. Oral contraceptive use may slightly increase your chance of having breast cancer diagnosed, particularly after using hormonal contraceptives at a younger age. After you stop using hormonal contraceptives, the chances of getting breast cancer begin to go back down. You should have regular breast examinations by a healthcare provider and examine your own breasts monthly. Tell your healthcare provider if you have a family history of breast cancer or if you have had breast nodules or an abnormal mammogram. Women who currently have or have had breast cancer should not use oral contraceptives because breast cancer is a hormone-sensitive tumor.

Some studies have found an increase in the incidence of cancer of the cervix in women who use oral contraceptives. However, this finding may be related to factors other than the use of oral contraceptives.

ESTIMATED RISK OF DEATH FROM A BIRTH CONTROL METHOD OR PREGNANCY

All methods of birth control and pregnancy are associated with a risk of developing certain diseases which may lead to disability or death. An estimate of the number of deaths associated with different methods of birth control and pregnancy has been calculated and is shown in the following table.

ANNUAL NUMBER OF BIRTH-RELATED OR METHOD-RELATED DEATHS ASSOCIATED WITH CONTROL OF FERTILITY PER 100,000 NONSTERILE WOMEN, BY FERTILITY-CONTROL METHOD ACCORDING TO AGE
Method of Control and Outcome | 15–19 | 20–24 | 25–29 | 30–34 | 35–39 | 40–44
No fertility control methods [Deaths are birth-related] | 7 | 7.4 | 9.1 | 14.8 | 25.7 | 28.2
Oral contraceptives nonsmoker [Deaths are method-related] | 0.3 | 0.5 | 0.9 | 1.9 | 13.8 | 31.6
Oral contraceptives smoker | 2.2 | 3.4 | 6.6 | 13.5 | 51.1 | 117.2
lUD | 0.8 | 0.8 | 1 | 1 | 1.4 | 1.4
Condom | 1.1 | 1.6 | 0.7 | 0.2 | 0.3 | 0.4
Diaphragm/spermicide | 1.9 | 1.2 | 1.2 | 1.3 | 2.2 | 2.8
Periodic abstinence | 2.5 | 1.6 | 1.6 | 1.7 | 2.9 | 3.6
Adapted from H.W. Ory, Family Planning Perspectives 15:57-63, 1983.

In the above table, the risk of death from any birth-control method is less than the risk of childbirth, except for oral contraceptive users over the age of 35 who smoke and pill users over the age of 40 even if they do not smoke. It can be seen in the table that for women aged 15 to 39, the risk of death was highest with pregnancy (7–26 deaths per 100,000 women, depending on age). Among pill users who do not smoke, the risk of death was always lower than that associated with pregnancy for any age group, except for those women over the age of 40, when the risk increases to 32 deaths per 100,000 women, compared to 28 associated with pregnancy at that age. However, for pill users who smoke and are over the age of 35, the estimated number of deaths exceeds those for other methods of birth control. If a woman is over the age of 40 and smokes, her estimated risk of death is four times higher (117/100,000 women) than the estimated risk associated with pregnancy (28/100,000 women) in that age group.

The suggestion that women over 40 who do not smoke should not take oral contraceptives is based on information from older high-dose pills and on less-selective use of pills than is practiced today. An Advisory Committee of the FDA discussed this issue in 1989 and recommended that the benefits of oral contraceptive use by healthy, non-smoking women over 40 years of age may outweigh the possible risks. However, all women, especially older women, are cautioned to use the lowest-dose pill that is effective.

WARNING SIGNALS

If any of these adverse effects occur while you are taking oral contraceptives, call your doctor immediately:

- Sharp chest pain, coughing of blood, or sudden shortness of breath (indicating a possible clot in the lung)
- Pain in the calf (indicating a possible clot in the leg)
- Crushing chest pain or heaviness in the chest (indicating a possible heart attack)
- Sudden severe headache or vomiting, dizziness or fainting, disturbances of vision or speech, weakness, or numbness in an arm or leg (indicating a possible stroke)
- Sudden partial or complete loss of vision (indicating a possible clot in the eye)
- Breast lumps (indicating possible breast cancer or fibrocystic disease of the breast; ask your doctor or healthcare provider to show you how to examine your breasts)
- Severe pain or tenderness in the stomach area (indicating a possibly ruptured liver tumor)
- Difficulty in sleeping, weakness, lack of energy, fatigue, or change in mood (possibly indicating severe depression)
- Jaundice or a yellowing of the skin or eyeballs, accompanied frequently by fever, fatigue, loss of appetite, dark-colored urine, or light-colored bowel movements (indicating possible liver problems)

SIDE EFFECTS OF ORAL CONTRACEPTIVES

1. VAGINAL BLEEDING

Irregular vaginal bleeding or spotting may occur while you are taking the pills. Irregular bleeding may vary from slight staining between menstrual periods to breakthrough bleeding, which is a flow much like a regular period. Irregular bleeding occurs most often during the first few months of oral contraceptive use, but may also occur after you have been taking the pill for some time. Such bleeding may be temporary and usually does not indicate any serious problems. It is important to continue taking your pills on schedule. If the bleeding occurs in more than one cycle or lasts for more than a few days, talk to your doctor or healthcare provider.

2. CONTACT LENSES

If you wear contact lenses and notice a change in vision or an inability to wear your lenses, contact your doctor or healthcare provider.

3. FLUID RETENTION

Oral contraceptives may cause edema (fluid retention) with swelling of the fingers or ankles and may raise your blood pressure. If you experience fluid retention, contact your doctor or healthcare provider.

4. MELASMA

A spotty darkening of the skin is possible, particularly of the face.

5. OTHER SIDE EFFECTS

Other side effects may include nausea, vomiting, change in appetite, headache, nervousness, depression, dizziness, loss of scalp hair, rash, and vaginal infections.

If any of these side effects occur, call your doctor or healthcare provider.

GENERAL PRECAUTIONS

1. Missed periods and use of oral contraceptives before or during early pregnancy.

There may be times when you may not menstruate regularly after you have completed taking a cycle of pills. If you have taken your pills regularly and miss one menstrual period, continue taking your pills for the next cycle but be sure to inform your healthcare provider before doing so. If you have not taken the pills daily as instructed and missed a menstrual period, or if you missed two consecutive menstrual periods, you may be pregnant. Check with your healthcare provider immediately to determine whether you are pregnant. Stop taking oral contraceptives if pregnancy is confirmed.

There is no conclusive evidence that oral contraceptive use is associated with an increase in birth defects when taken inadvertently during early pregnancy. Previously, a few studies had reported that oral contraceptives might be associated with birth defects, but these studies have not been confirmed. Nevertheless, oral contraceptives should not be used during pregnancy. You should check with your doctor about risks to your unborn child of any medication taken during pregnancy.

2. While Breast-Feeding

If you are breast-feeding, consult your doctor before starting oral contraceptives. Some of the drug will be passed on to the child in the milk. A few adverse effects on the child have been reported, including yellowing of the skin (jaundice) and breast enlargement. In addition, oral contraceptives may decrease the amount and quality of your milk. If possible, do not use oral contraceptives while breast-feeding. You should use another method of contraception since breast-feeding provides only partial protection from becoming pregnant, and this partial protection decreases significantly as you breast-feed for longer periods of time. You should consider starting oral contraceptives only after you have weaned your child completely.

3. Laboratory Tests

If you are scheduled for any laboratory tests, tell your doctor you are taking birth-control pills. Certain blood tests may be affected by birth-control pills.

4. Drug Interactions

Certain drugs may interact with birth-control pills to make them less effective in preventing pregnancy or cause an increase in breakthrough bleeding. Such drugs include rifampin, drugs used for epilepsy such as barbiturates (for example, phenobarbital) and phenytoin (Dilantin is one brand of this drug), phenylbutazone (Butazolidin is one brand) and possibly certain antibiotics. Herbal products containing St. John's Wort (hypericum perforatum) may reduce the effectiveness of oral contraceptives. This may also result in breakthrough bleeding. You may need to use an additional method of contraception during any cycle in which you take drugs that can make oral contraceptives less effective (also See BOLDED TEXT AT BEGINNING).

5. Sexually Transmitted Diseases

This product (like all oral contraceptives) is intended to prevent pregnancy. It does not protect against transmission of HIV (AIDS) and other sexually transmitted diseases such as chlamydia, genital herpes, genital warts, gonorrhea, hepatitis B, and syphilis.

HOW TO TAKE THE PILL

IMPORTANT POINTS TO REMEMBER

BEFORE YOU START TAKING YOUR PILLS

1. BE SURE TO READ THESE DIRECTIONS:

Before you start taking your pills.

Any time you are not sure what to do.

2. THE RIGHT WAY TO TAKE THE PILL IS TO TAKE ONE PILL EVERY DAY AT THE SAME TIME.

If you miss pills you could get pregnant. This includes starting the pack late. The more pills you miss, the more likely you are to get pregnant.

3. MANY WOMEN HAVE SPOTTING OR LIGHT BLEEDING, OR MAY FEEL SICK TO THEIR STOMACH DURING THE FIRST 1–3 PACKS OF PILLS.

If you do have spotting or light bleeding or feel sick to your stomach, do not stop taking the pill. The problem will usually go away. If it does not go away, check with your doctor or healthcare provider.

4. MISSING PILLS CAN ALSO CAUSE SPOTTING OR LIGHT BLEEDING, even when you make up these missed pills.

On the days you take two pills, to make up for missed pills, you could also feel a little sick to your stomach.

5. IF YOU HAVE VOMITING OR DIARRHEA, for any reason, or IF YOU TAKE SOME MEDICINES, including some antibiotics and some herbal products such as St. John's Wort, your pills may not work as well.

Use a back-up method (such as condoms or spermicides) until you check with your doctor or healthcare provider.

6. IF YOU HAVE TROUBLE REMEMBERING TO TAKE THE PILL, talk to your doctor or healthcare provider about how to make pill-taking easier or about using another method of birth control.

7. IF YOU HAVE ANY QUESTIONS OR ARE UNSURE ABOUT THE INFORMATION IN THIS LEAFLET, call your doctor or healthcare provider.

BEFORE YOU START TAKING YOUR PILLS

1. DECIDE WHAT TIME OF DAY YOU WANT TO TAKE YOUR PILL.
It is important to take it at about the same time every day.

2. LOOK AT YOUR PILL PACK - IT HAS 28 PILLS: The OCELLA pill pack has 21 yellow "active" pills (with hormones) to be taken for three weeks, followed by 7 white "reminder" pills (without hormones) to be taken for one week.

3. ALSO FIND:

1) where on the pack to start taking pills,

2) in what order to take the pills (follow the arrows)

3) the week numbers as shown in the diagram below

4. BE SURE YOU HAVE READY AT ALL TIMES:

ANOTHER KIND OF BIRTH CONTROL (such as condoms or spermicides) to use as a back-up in case you miss pills.

AN EXTRA, FULL PILL PACK.

WHEN TO START THE FIRST PACK OF PILLS

You have a choice for which day to start taking your first pack of pills. Decide with your doctor or healthcare provider which is the best day for you. Pick a time of day which will be easy to remember.

DAY 1 START:

1. Take the first yellow "active" pill of the first pack during the first 24 hours of your period.
2. You will not need to use a back-up method of birth control, since you are starting the pill at the beginning of your period.

SUNDAY START:

1. Take the first yellow "active" pill of the first pack on the Sunday after your period starts, even if you are still bleeding. If your period begins on Sunday, start the pack that same day.
2. Use another method of birth control (such as condoms or spermicides) as a back-up method if you have sex any time from the Sunday you start your first pack until the next Sunday (7 days).

WHAT TO DO DURING THE MONTH

1. TAKE ONE PILL AT THE SAME TIME EVERY DAY UNTIL THE PACK IS EMPTY Do not skip pills even if you are spotting or bleeding between monthly periods or feel sick to your stomach (nausea).
2. Do not skip pills even if you do not have sex very often.
3. WHEN YOU FINISH A PACK OR SWITCH YOUR BRAND OF PILLS: Start the next pack on the day after your last white "reminder" pill. Do not wait any days between packs.

WHAT TO DO IF YOU MISS PILLS

If you MISS 1 yellow "active" pill:

1. Take it as soon as you remember. Take the next pill at your regular time. This means you may take two pills in one day.
2. You do not need to use a back-up birth control method if you have sex.

If you MISS 2 yellow "active" pills in a row in WEEK 1 OR WEEK 2 of your pack:

1. Take two pills on the day you remember and two pills the next day.
2. Then take one pill a day until you finish the pack.
3. You MAY BECOME PREGNANT if you have sex in the 7 days after you miss pills. You MUST use another birth control method (such as condoms or spermicides) as a back-up for those 7 days.

If you MISS 2 yellow "active" pills in a row in the 3RD WEEK:

1. If you are a Day 1 Starter:

THROW OUT the rest of the pill pack and start a new pack that same day.

If you are a Sunday Starter:

Keep taking one pill every day until Sunday. On Sunday, THROW OUT the rest of the pack and start a new pack of pills that same day.

2. You may not have your period this month but this is expected. However, if you miss your period two months in a row, call your doctor or healthcare provider because you might be pregnant.

3. You MAY BECOME PREGNANT if you have sex in the 7 days after you miss pills. You MUST use another birth control method (such as condoms or spermicides) as a back-up for those 7 days.

If you MISS 3 OR MORE yellow "active" pills in a row (during the first 3 weeks).

1. If you are a Day 1 Starter:

THROW OUT the rest of the pill pack and start a new pack that same day.

If you are a Sunday Starter:

Keep taking 1 pill every day until Sunday. On Sunday, THROW OUT the rest of the pack and start a new pack of pills that same day.

2. You may not have your period this month but this is expected. However, if you miss your period two months in a row, call your doctor or healthcare provider because you might be pregnant.

3. You MAY BECOME PREGNANT if you have sex in the 7 days after you miss pills. You MUST use another birth control method (such as condoms or spermicides) as a back-up for those 7 days.

If you forget any of the 7 white "reminder" pills in Week 4:

THROW AWAY the pills you missed.

Keep taking one pill each day until the pack is empty.

You do not need a back-up method.

FINALLY, IF YOU ARE STILL NOT SURE WHAT TO DO ABOUT THE PILLS YOU HAVE MISSED:

Use a BACK-UP METHOD (such as condoms or spermicides) any time you have sex.

KEEP TAKING ONE ACTIVE PILL EACH DAY until you can reach your doctor or healthcare provider.

PREGNANCY DUE TO PILL FAILURE

The incidence of pill failure resulting in pregnancy is approximately less than 1% (one pregnancy per 100 women per year of use) if taken every day as directed, but more typical failure rates are about 5%. If failure does occur with OCELLA use, the risk to the fetus is unknown.

PREGNANCY AFTER STOPPING THE PILL

There may be some delay in becoming pregnant after you stop using oral contraceptives, especially if you had irregular menstrual cycles before you used oral contraceptives. It may be advisable to postpone conception until you begin menstruating regularly once you have stopped taking the pill and desire pregnancy.

There does not appear to be any increase in birth defects in newborn babies when pregnancy occurs soon after stopping the pill.

OVERDOSAGE

Serious ill effects have not been reported following ingestion of large doses of other oral contraceptives by young children. Overdosage of OCELLA may cause nausea and withdrawal bleeding in females and may increase blood levels of potassium or decrease blood levels of sodium, which could be dangerous. In case of overdosage, contact your healthcare provider.

OTHER INFORMATION

Your healthcare provider will take a medical and family history before prescribing oral contraceptives and will examine you. The physical examination may be delayed to another time if you request it and the healthcare provider believes that it is appropriate to postpone it. You should be re-examined at least once a year. Be sure to inform your healthcare provider if there is a family history of any of the conditions listed previously in this leaflet. Be sure to keep all appointments with your healthcare provider, because this is a time to determine if there are early signs of side effects of oral contraceptive use.

Do not use the drug for any condition other than the one for which it was prescribed. This drug has been prescribed specifically for you; do not give it to others who may want birth-control pills.

HEALTH BENEFITS FROM ORAL CONTRACEPTIVES

In addition to preventing pregnancy, use of oral contraceptives may provide certain benefits. They are:

- Menstrual cycles may become more regular
- Blood flow during menstruation may be lighter and less iron may be lost. Therefore, anemia due to iron deficiency is less likely to occur.
- Pain or other symptoms during menstruation may be encountered less frequently
- Ovarian cysts may occur less frequently
- Ectopic (tubal) pregnancy may occur less frequently
- Noncancerous cysts or lumps in the breast may occur less frequently
- Acute pelvic inflammatory disease may occur less frequently
- Oral contraceptive use may provide some protection against developing two forms of cancer: cancer of the ovaries and cancer of the lining of the uterus

If you want more information about birth-control pills, ask your doctor or pharmacist. They have a more technical leaflet called the Prescribing Information which you may wish to read.

Mfd.for Barr Laboratories, Inc., Pomona, NY 10970

by Bayer HealthCare Pharmacueticals Inc., Wayne, NJ 07470

Made in Germany

810413xx Month 2010

Principal Display Panel

NDC 54868-5922-0

OCELLA

(drospirenone and ethinyl estradiol tablets) 3 mg/0.03 mg

This product (like all oral contraceptives) is intended to prevent pregnancy. It does not protect against HIV infection (AIDS) and other sexually transmitted diseases.

Store at 25°C with excursions permitted between 15–30°C. [See USP Controlled Room Temperature].

To the Dispenser: This unit contains two pieces of information intended for the patient, which are combined in a single booklet. This informational piece is to be provided to the patient with each prescription.

Rx only